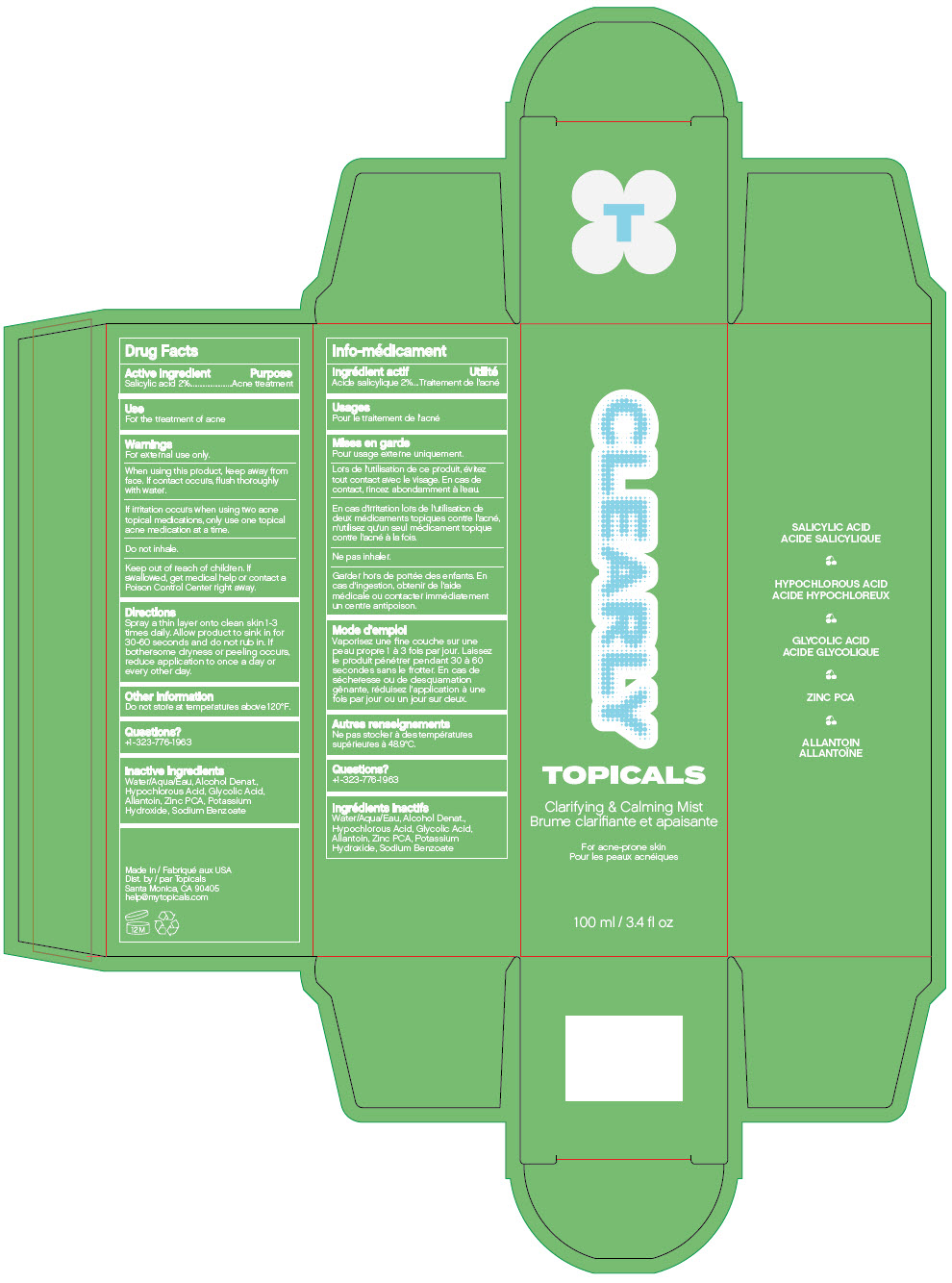 DRUG LABEL: Topicals Clearly Mist
NDC: 51326-307 | Form: LIQUID
Manufacturer: Topiderm, Inc.
Category: otc | Type: HUMAN OTC DRUG LABEL
Date: 20240924

ACTIVE INGREDIENTS: SALICYLIC ACID 20 mg/1 mL
INACTIVE INGREDIENTS: WATER; ALCOHOL; HYPOCHLOROUS ACID; GLYCOLIC ACID; ALLANTOIN; ZINC PIDOLATE; POTASSIUM HYDROXIDE; SODIUM BENZOATE

Topicals Clearly Mist

Drug Facts

Active ingredient

Salicylic acid 2%

Purpose

Acne treatment

Use

For the treatment of acne

Warnings

For external use only.

When using this product, keep away from face. If contact occurs, flush thoroughly with water.

If irritation occurs when using two acne topical medications, only use one topical acne medication at a time.

Do not inhale.

Keep out of reach of children. If swallowed, get medical help or contact a Poison Control Center right away.

Directions

Spray a thin layer onto clean skin 1-3 times daily. Allow product to sink in for 30-60 seconds and do not rub in. If bothersome dryness or peeling occurs, reduce application to once a day or every other day.

Other information

Do not store at temperatures above 120°F.

Questions?

+1-323-776-1963

Inactive ingredients

Water/Aqua/Eau, Alcohol Denat., Hypochlorous Acid, Glycolic Acid, Allantoin, Zinc PCA, Potassium Hydroxide, Sodium Benzoate

Dist. by Topicals
Santa Monica, CA 90405

PRINCIPAL DISPLAY PANEL - 100 ml Bottle Carton

CLEARLY

TOPICALS

Clarifying & Calming Mist

For acne-prone skin

100 ml / 3.4 fl oz